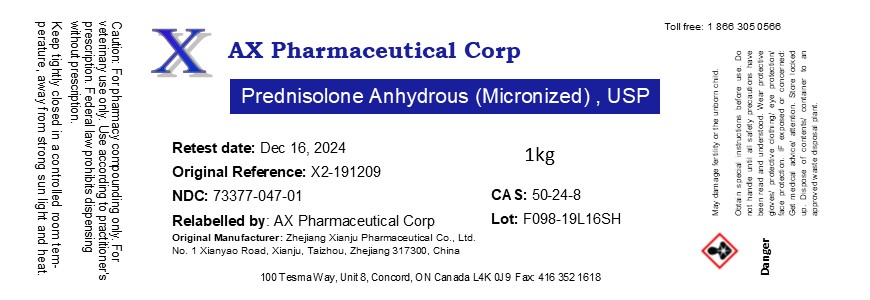 DRUG LABEL: Prednisolone anhydrous Micronized
NDC: 73377-047 | Form: POWDER
Manufacturer: AX Pharmaceutical Corp
Category: other | Type: BULK INGREDIENT - ANIMAL DRUG
Date: 20231208

ACTIVE INGREDIENTS: PREDNISOLONE 1 kg/1 kg

Prednisolone anhydrous Micronized